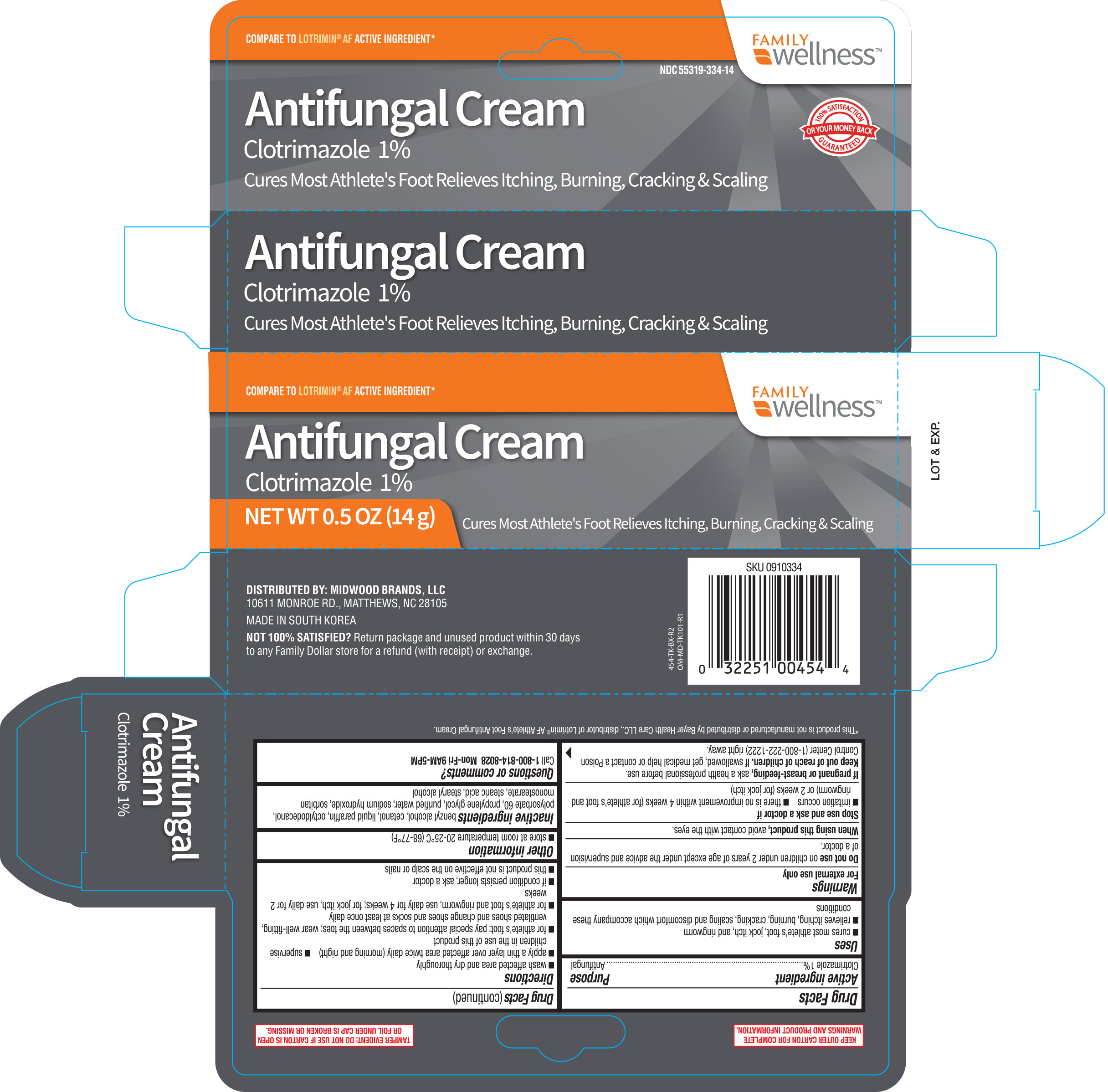 DRUG LABEL: Family Wellness Antifungal
NDC: 55319-334 | Form: CREAM
Manufacturer: Family Dollar
Category: otc | Type: HUMAN OTC DRUG LABEL
Date: 20181220

ACTIVE INGREDIENTS: CLOTRIMAZOLE 10 mg/1 g
INACTIVE INGREDIENTS: CETYL ALCOHOL; MINERAL OIL; STEARYL ALCOHOL; OCTYLDODECANOL; BENZYL ALCOHOL; POLYSORBATE 60; PROPYLENE GLYCOL; WATER; SORBITAN MONOSTEARATE; STEARIC ACID; SODIUM HYDROXIDE

Family Wellness Anti-Fungal Cream Clotrimazole 1% 0.5oz (454, 2018)

Active Ingredient Purpose

Clotrimazole 1%............................................... Antifungal

Uses

- Cures most athlete's foot, jock itch, and ringworm
- Relieves itching, burning, cracking, scaling, and discomfort which accompany these conditions

Warnings

For external use only.

Do not use on children under 2 years of age except under the advice and supervision of a doctor

When using this product avoid contact with eyes.

Stop use and ask a doctor if

- irritation occurs
- there is no improvement within 4 weeks (for athlete's foot and ringworm) or 2 weeks (for jock itch)

PREGNANCY OR BREAST FEEDING

If pregnant or breast-feeding, ask a health professional before use.

Keep out of reach of children. If swallowed, get medical help or contact a Poision Control Center (1-800-222-1222) right away.

Directions

- Wash affected area and dry thoroughly
- Apply a thin layer over affected area twice daily (morning and night)
- Supervise children in the use of this product
- For athlete's foot, pay special attention to spaces between the toes, wear well-fitting, ventilated shoes and change shoes and socks at least once a day
- For athlete's foot and ringworm use daily for 4 weeks, for jock itch use daily for 2 weeks
- If condition persists longer, ask a doctor
- This product is no effective on the scalp or nails

Other information

- Store between 20-25°C (68-77°F)

Inactive ingredients

benzyl alcohol, cetanol, liquid paraffin, octyldodecanol, polysorbate 60, proylene glycol, purified water, sodium hydroxide, sorbitan monostearate, stearic acid, stearyl alcohol

Questions or comments?

Call 1-800-814-8028 Mon-Fri 9AM-5PM

DOSAGE AND ADMINISTRATION

DISTRIBUTED BY: MIDWOOD BRANDS, LLC

10611 MONROE RD., MATTHEWS, NC 28105

MADE IN SOUTH KOREA